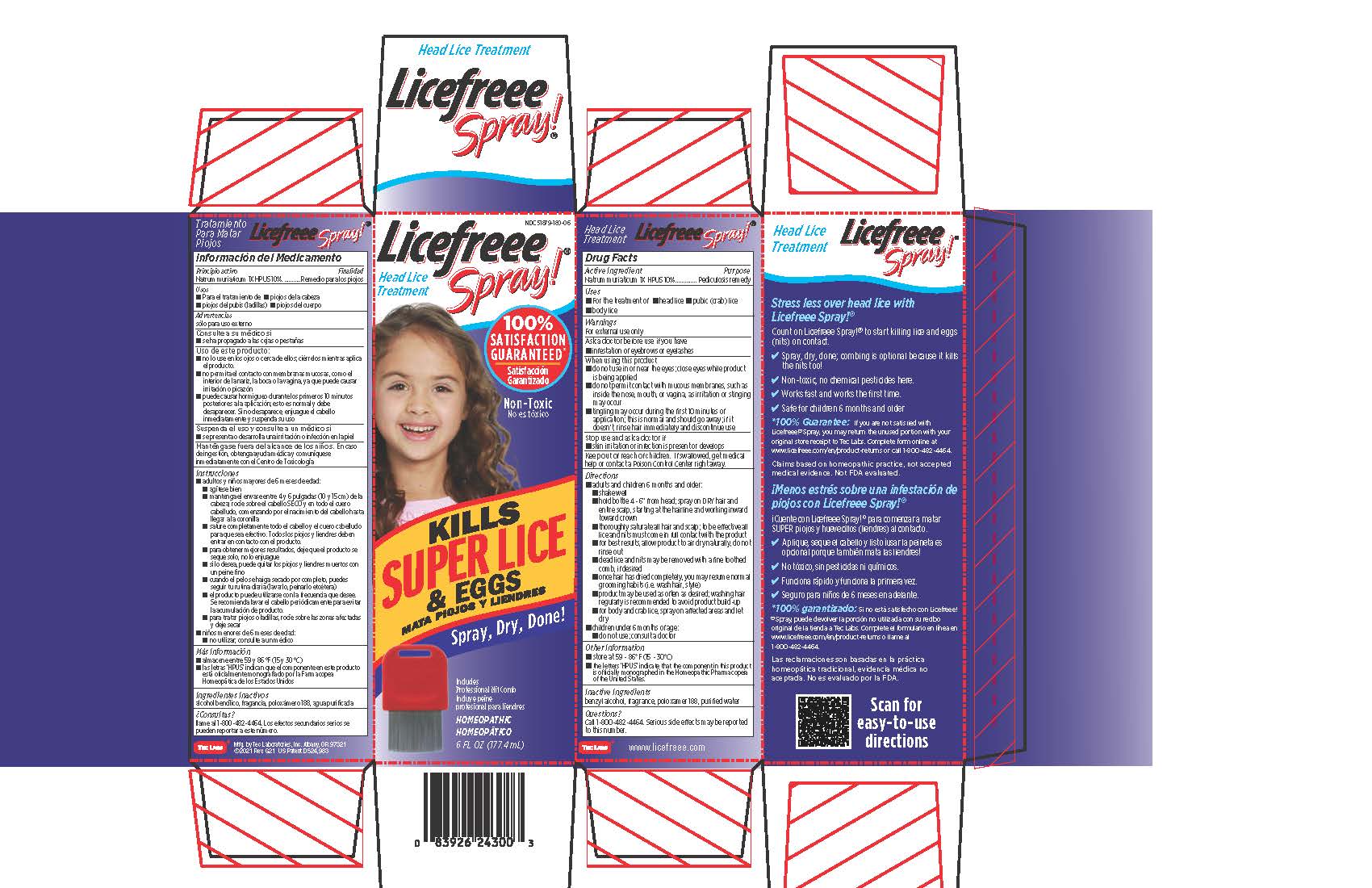 DRUG LABEL: Licefreee
NDC: 51879-180 | Form: SPRAY
Manufacturer: Tec Laboratories, Inc.
Category: homeopathic | Type: HUMAN OTC DRUG LABEL
Date: 20241105

ACTIVE INGREDIENTS: SODIUM CHLORIDE 1 [hp_X]/1 mL
INACTIVE INGREDIENTS: WATER; POLOXAMER 188; BENZYL ALCOHOL

LiceFreee Spray

ACTIVE INGREDIENT

Natrum muriaticum 1X

(Sodium chloride, USP)

PURPOSE

Peduculosis remedy

Uses

- For the treatment of •head lice •pubic (crab) lice •body lice

Warnings

For external use only

When using this product

- do not use in or near the eyes; close eyes while product is being applied
- do not permit contact with mucous membranes, such as inside the nose, mouth, or vagina, as irritation or stinging may occur
- tingling may occur during the first 10 minutes of application; this is normal and should go away; if it doesn't, rinse hair immediately and discontinue use

Stop use and ask a doctor if

- skin irritation or infection is present or develops

Keep out of reach of children.If swallowed, get medical help or contact a Poison Control Center right away.

Inactive ingredients

benzyl alcohol, fragrance, poloxamer 188, purified water

Questions?

Call 1-800-482-4464. Serious side effects may be reported to this number

Directions

- Adults and children 6 months and older:
- shake well
- hold bottle 4 - 6" from head; spray on DRY hair and entire scalp, starting at the hairline and working inward toward crown
- thoroughly saturate all hair and scalp; to be effective all lice and nits must come in full contact with the product
- dead lice and nits may be removed with a fine toothed comb, if desired
- for best results, allow product to air dry naturally, do not rinse out
- product may be used as often as desired; washing hair regularly is recommended to avoid product build-up
- for body and crab lice, spray on affected areas and let dry
- Children under 6 months of age:
- do not use; consult a doctor

PACKAGE LABEL

NDC 51879-180-06

Licefreee Spray! (R)

Instant Head Lice Treatment

Kills lice and eggs on contact

Mata piojos y liendres al contacto

Non-Toxic One Easy Step

No ex toxico Un paso facil

100% Guaranteed

Garantizado

Includes Professional Nit Comb

Incluye peine profesional para liendres

Homeopathic

Homeopatica

NET 6 FL OZ (177.4 mL)